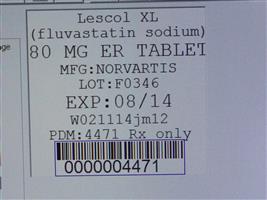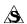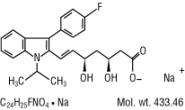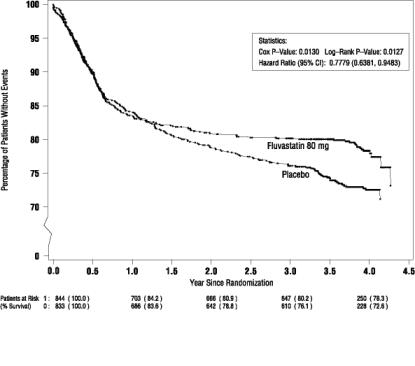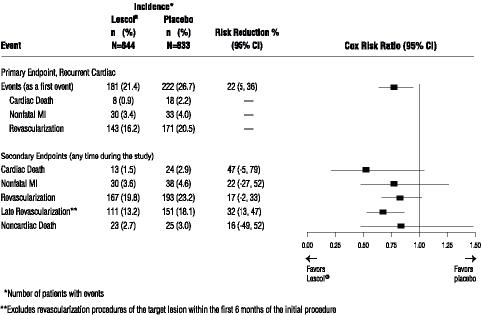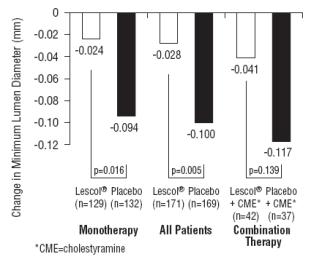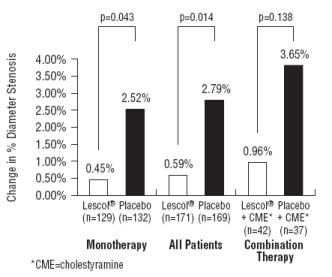 DRUG LABEL: Lescol
                                    
NDC: 68151-4471 | Form: TABLET, EXTENDED RELEASE
Manufacturer: Carilion Materials Management
Category: prescription | Type: HUMAN PRESCRIPTION DRUG LABEL
Date: 20121031

ACTIVE INGREDIENTS: FLUVASTATIN SODIUM 80 mg/1 1
INACTIVE INGREDIENTS: HYDROXYPROPYL CELLULOSE (TYPE H); HYPROMELLOSE 2208 (15000 MPA.S); FERRIC OXIDE YELLOW; MAGNESIUM STEARATE; CELLULOSE, MICROCRYSTALLINE; POLYETHYLENE GLYCOL 8000; POTASSIUM BICARBONATE; POVIDONES; TITANIUM DIOXIDE

HIGHLIGHTS OF PRESCRIBING INFORMATION

These highlights do not include all the information needed to use Lescol®/ Lescol® XL safely and effectively. See full prescribing information for Lescol®/ Lescol® XL.
Lescol® (fluvastatin sodium) capsules/ Lescol® XL (fluvastatin sodium) extended-release tablets for oral use
Initial U.S. Approval: 1993/ 2000

1 INDICATIONS AND USAGE

LESCOL/LESCOL XL is an HMG-CoA reductase inhibitor (statin) indicated as an adjunctive therapy to diet to:

- Reduce elevated TC, LDL-C, Apo B, and TG, and to increase HDL-C in adult patients with primary hypercholesterolemia and mixed dyslipidemia () 1.1
- Reduce elevated TC, LDL-C, and Apo B levels in boys and post-menarchal girls, 10 to 16 years of age, with heterozygous familial hypercholesterolemia after failing an adequate trial of diet therapy () 1.1
- Reduce the risk of undergoing revascularization procedures in patients with clinically evident CHD () 1.2
- Slow the progression of atherosclerosis in patients with CHD () 1.2

Limitations of Use:

- Neither LESCOL nor LESCOL XL have been studied in conditions where the major abnormality is elevation of chylomicrons, VLDL, or IDL (i.e., hyperlipoproteinemia Types I, III, IV, or V) () 1.3

2 DOSAGE AND ADMINISTRATION

- Dose range: 20 mg to 80 mg/ day () 2.1
- LESCOL/LESCOL XL can be taken with or without food. Only LESCOL XL may be taken at any time of the day () 2.1
- Do not break, crush or chew LESCOL XL tablets or open LESCOL capsules prior to administration () 2.1
- Adults: the recommended starting dose is 40 mg to 80 mg (administered as one LESCOL 40 mg capsule twice daily, or one 80 mg LESCOL XL once daily) () 2.2
- Do not take two LESCOL 40 mg capsules at one time
- Children with heterozygous familial hypercholesterolemia (ages 10 to 16, inclusive): the recommended starting dose is LESCOL capsule 20 mg once daily () 2.3

3 DOSAGE FORMS AND STRENGTHS

LESCOL Capsules: 20 mg, 40 mg;

LESCOL XL Tablets: 80 mg () 3

4 CONTRAINDICATIONS

- Hypersensitivity to any component of this medication () 4
- Active liver disease or unexplained, persistent elevations in serum transaminases (,) 45.2
- Women who are pregnant or may become pregnant (,) 48.1
- Nursing mothers (,) 48.3

5 WARNINGS AND PRECAUTIONS

- Risks increase with advanced age (65), uncontrolled hypothyroidism, renal impairment, and combination use with cyclosporine,or gemfibrozil. Advise patients to promptly report to their physician unexplained and/or persistent muscle pain, tenderness, or weakness and discontinue LESCOL/LESCOL XL if myopathy is diagnosed or suspected. (, ,) Skeletal muscle effects (e.g. myopathy and rhabdomyolysis):>5.18.58.7
- Patients should be advised to report promptly any symptoms of myopathy. LESCOL/LESCOL XL therapy should be discontinued if myopathy is diagnosed or suspected () 5.1
- Persistent elevations in hepatic transaminases can occur. Check liver enzyme tests before initiating therapy and as clinically indicated thereafter () Liver enzyme abnormalities:5.2

6 ADVERSE REACTIONS

Most frequent adverse reactions (rate ≥2% and > placebo) are: headache, dyspepsia, myalgia, abdominal pain and nausea () 6.1

To report SUSPECTED ADVERSE REACTIONS, contact Novartis Pharmaceuticals Corporation at 1-888-669-6682 or FDA at 1-800-FDA-1088 or www.fda.gov/medwatch.

7 DRUG INTERACTIONS

- : Combination increases fluvastatin exposure. Limit LESCOL dose to 20 mg (,) Cyclosporine 2.47.1
- : Combination increases fluvastatin exposure. Limit LESCOL dose to 20 mg (,) Fluconazole 2.57.2
- Use with fibrates or lipid-modifying doses (≥1 g/day) of niacin increases the risk of adverse skeletal muscle effects. Caution should be used when prescribing with LESCOL/LESCOL XL (, ,) Concomitant lipid-lowering therapies:5.17.37.4
- Monitor blood glucose levels when fluvastatin dose is changed () Glyburide:7
- Monitor plasma phenytoin levels when fluvastatin treatment is initiated or when the dosage is changed () Phenytoin:7
- Monitor prothrombin times when fluvastatin co-administration is initiated, discontinued, or the dosage changed () Warfarin andcoumarinderivates:7

FULL PRESCRIBING INFORMATION

1 INDICATIONS AND USAGE

Therapy with lipid-altering agents should be only one component of multiple risk factor intervention in individuals at significantly increased risk for atherosclerotic vascular disease due to hypercholesterolemia. Drug therapy is indicated as an adjunct to diet when the response to a diet restricted in saturated fat and cholesterol and other non-pharmacologic measures alone has been inadequate.

1.1 Hypercholesterolemia (Heterozygous Familial and Nonfamilial) and Mixed Dyslipidemia

LESCOL and LESCOL XL are indicated

- as an adjunct to diet to reduce elevated total cholesterol (Total-C), low-density lipoprotein cholesterol (LDL-C), triglyceride (TG) and apolipoprotein B (Apo B) levels, and to increase high-density lipoprotein cholesterol (HDL-C) in patients with primary hypercholesterolemia and mixed dyslipidemia (Fredrickson Type IIa and IIb).
- as an adjunct to diet to reduce Total-C, LDL-C, and Apo B levels in adolescent boys and adolescent girls who are at least one year post-menarche, 10-16 years of age, with heterozygous familial hypercholesterolemia and the following findings are present:
  - LDL-C remains ≥ 190 mg/dL or
  - LDL-C remains ≥ 160 mg/dL and:
    - there is a positive family history of premature cardiovascular disease or
    - two or more other cardiovascular disease risk factors are present

The NCEP classification of cholesterol levels in pediatric patients with a familial history of hypercholesterolemia or premature CVD is summarized below.

Category | Total-C (mg/dL) | LDL-C (mg/dL)
Acceptable | <170 | <110
Borderline | 170-199 | 110-129
High | ≥200 | ≥130

Children treated with fluvastatin in adolescence should be re-evaluated in adulthood and appropriate changes made to their cholesterol-lowering regimen to achieve adult treatment goals.

1.2 Secondary Prevention of Cardiovascular Disease

In patients with clinically evident CHD, LESCOL and LESCOL XL are indicated to:

- reduce the risk of undergoing coronary revascularization procedures
- slow the progression of coronary atherosclerosis

1.3 Limitations of Use

Neither LESCOL nor LESCOL XL have been studied in conditions where the major abnormality is elevation of chylomicrons, VLDL, or IDL (i.e., hyperlipoproteinemia Types I, III, IV, or V).

2 DOSAGE AND ADMINISTRATION

2.1 General Dosing Information

Dose range: 20 mg to 80 mg/ day.

LESCOL/LESCOL XL can be administered orally as a single dose, with or without food.

Do not break, crush or chew LESCOL XL tablets or open LESCOL capsules prior to administration.

Do not take two LESCOL 40 mg capsules at one time.

Since the maximal effect of a given dose is seen within 4 weeks, periodic lipid determinations should be performed at this time and dosage adjusted according to the patient’s response to therapy and established treatment guidelines.

For patients requiring LDL-C reduction to a goal of ≥25%, the recommended starting dose is 40 mg as one capsule in the evening, 80 mg as one LESCOL XL tablet administered as a single dose at any time of the day or 80 mg in divided doses of the 40 mg capsule given twice daily. For patients requiring LDL-C reduction to a goal of <25% a starting dose of 20 mg may be used.

2.2 Adult Patients with Hypercholesterolemia (Heterozygous Familial and Nonfamilial) and Mixed Dyslipidemia

Adult patients can be started on either LESCOL or LESCOL XL. The recommended starting dose for LESCOL is one 40 mg capsule in the evening, or one LESCOL 40 mg capsule twice daily. Do not take two LESCOL 40 mg capsules at one time.

The recommended starting dose for LESCOL XL is one 80 mg tablet administered as a single dose at any time of the day.

2.3 Pediatric Patients (10-16 years of age) with Heterozygous Familial Hypercholesterolemia

The recommended starting dose is one 20 mg LESCOL capsule. Dose adjustments, up to a maximum daily dose administered either as LESCOL capsules 40 mg twice daily or one LESCOL XL 80 mg tablet once daily should be made at 6 week intervals. Doses should be individualized according to the goal of therapy [ ] . see NCEP Pediatric Panel Guidelines and CLINICAL STUDIES (14)^1

National Cholesterol Education Program (NCEP): Highlights of the Report of the Expert Panel on Blood Cholesterol Levels in Children and Adolescents. 89(3):495-501. 1992.^1 Pediatrics.

2.4 Use with Cyclosporine

Do not exceed a dose of 20 mg b.i.d. LESCOL in patients taking cyclosporine . [see Drug Interactions 7.1]

2.5 Use with Fluconazole

Do not exceed a dose of 20 mg b.i.d. LESCOL in patients taking fluconazole . [see Drug Interactions 7.2]

3 DOSAGE FORMS AND STRENGTHS

• LESCOL 20 mg capsules are brown and light brown imprinted twice with “ ” and “20” on one half and “LESCOL” and the LESCOL (fluvastatin sodium) logo twice on the other half of the capsule. ®

• LESCOL 40 mg capsules are brown and gold imprinted twice with “ ” and “40” on one half and “LESCOL” and the LESCOL (fluvastatin sodium) logo twice on the other half of the capsule. ®

• LESCOL XL 80 mg tablets are yellow, round, slightly biconvex film-coated tablet with beveled edges debossed with “LESCOL XL” on one side and “80” on the other.

4 CONTRAINDICATIONS

4.1 Hypersensitivity to any Component of this Medication

LESCOL and LESCOL XL are contraindicated in patients with hypersensitivity to any component of this medication.

4.2 Active Liver Disease

LESCOL and LESCOL XL are contraindicated in patients with active liver disease or unexplained, persistent elevations in serum transaminases [ ]. see Warnings and Precautions (5.2)

4.3 Pregnancy

LESCOL and LESCOL XL are contraindicated in women who are pregnant or may become pregnant. Serum cholesterol and triglycerides increase during normal pregnancy, and cholesterol or cholesterol derivatives are essential for fetal development. LESCOL and LESCOL XL may cause fetal harm when administered to pregnant women. Atherosclerosis is a chronic process and the discontinuation of lipid-lowering drugs during pregnancy should have little impact on the outcome of long-term therapy of primary hypercholesterolemia.

LESCOL and LESCOL XL should be administered to women of childbearing age only when such patients are highly unlikely to conceive and have been informed of the potential hazards If the patient becomes pregnant while taking this drug, LESCOL and LESCOL XL should be discontinued and the patient should be apprised of the potential hazard to the fetus [ ]. . see Use In Specific Populations (8.1)

4.4 Nursing Mothers

Fluvastatin is secreted into the breast milk of animals and because HMG-CoA reductase inhibitors have the potential to cause serious adverse reactions in nursing infants, women who require treatment with LESCOL or LESCOL XL should be advised not to breastfeed their infants [ ]. see Use In Specific Populations (8.3)

5 WARNINGS AND PRECAUTIONS

5.1 Skeletal Muscle

Rhabdomyolysis with acute renal failure secondary tomyoglobinuriahave been reported with LESCOL/LESCOL XLand other drugs in this class.

LESCOL/LESCOL XL should be prescribed with caution in patients with predisposing factors for myopathy. These factors include advanced age (>65 years), renal impairment, and inadequately treated hypothyroidism.

The risk of myopathy and/or rhabdomyolysis with statins is increased with concurrent therapy with cyclosporine, erythromycin, fibrates or niacin. Myopathy was not observed in a clinical trial in 74 patients involving patients who were treated with LESCOL/LESCOL XL together with niacin. Isolated cases of myopathy have been reported during post-marketing experience with concomitant administration of LESCOL/LESCOL XL and colchicine. No information is available on the pharmacokinetic interaction between LESCOL/LESCOL XL and colchicine.

Uncomplicated myalgia has also been reported in LESCOL-treated patients [ ]. In clinical trials, uncomplicated myalgia has been observed infrequently in patients treated with LESCOL at rates indistinguishable from placebo. Myopathy, defined as muscle aching or muscle weakness in conjunction with increases in CPK values to greater than 10 times the upper limit of normal, was <0.1% in fluvastatin clinical trials. Myopathy should be considered in any patient with diffuse myalgias, muscle tenderness or weakness, and/or marked elevation of CPK. see Adverse Reactions (6)

There have been rare reports of immune-mediated necrotizing myopathy (IMNM), an autoimmune myopathy, associated with statin use. IMNM is characterized by: proximal muscle weakness and elevated serum creatine kinase, which persist despite discontinuation of statin treatment; muscle biopsy showing necrotizing myopathy without significant inflammation; improvement with immunosuppressive agents.

All patients should be advised to promptly report to their physician unexplained muscle pain, tenderness, or weakness, particularly if accompanied by malaise or fever or if muscle signs and symptoms persist after discontinuing LESCOL/LESCOL XL.

LESCOL/LESCOL XL therapy should be discontinued if markedly elevated CPK levels occur or myopathy is diagnosed or suspected. LESCOL/LESCOL XL therapy should also be temporarily withheld in any patient experiencing an acute or serious condition predisposing to the development of renal failure secondary to rhabdomyolysis, e.g., sepsis; hypotension; major surgery; trauma; severe metabolic, endocrine, or electrolyte disorders; or uncontrolled epilepsy.

5.2 Liver Enzymes

Increases in serum transaminases (aspartate aminotransferase [AST]/serum glutamic-oxaloacetic transaminase, or alanine aminotransferase [ALT]/serum glutamic-pyruvic transaminase) have been reported with HMG-CoA reductase inhibitors, including LESCOL/LESCOL XL. In most cases, the elevations were transient and resolved or improved on continued therapy or after a brief interruption in therapy.

Approximately 1.1% of patients treated with LESCOL capsules in worldwide trials developed dose-related, persistent elevations of serum transaminase levels to more than 3 times the upper limit of normal. Fourteen of these patients (0.6%) were discontinued from therapy. In all clinical trials, a total of 33/2969 patients (1.1%) had persistent transaminase elevations with an average LESCOL exposure of approximately 71.2 weeks; 19 of these patients (0.6%) were discontinued. The majority of patients with these abnormal biochemical findings were asymptomatic.

In a pooled analysis of all placebo-controlled studies in which LESCOL capsules were used, persistent transaminase elevations (>3 times the upper limit of normal [ULN] on two consecutive weekly measurements) occurred in 0.2%, 1.5%, and 2.7% of patients treated with daily doses of 20, 40, and 80 mg (titrated to 40 mg twice daily) LESCOL capsules, respectively. Ninety-one percent of the cases of persistent liver function test abnormalities (20 of 22 patients) occurred within 12 weeks of therapy and in all patients with persistent liver function test abnormalities there was an abnormal liver function test present at baseline or by Week 8.

In the pooled analysis of the 24-week controlled trials, persistent transaminase elevation occurred in 1.9%, 1.8% and 4.9% of patients treated with LESCOL XL 80 mg, LESCOL 40 mg and LESCOL 40 mg twice daily, respectively. In 13 of 16 patients treated with LESCOL XL the abnormality occurred within 12 weeks of initiation of treatment with LESCOL XL 80 mg.

It is recommended that liver enzyme tests be performed prior to the initiation of LESCOL/LESCOL XL, and if signs or symptoms of liver injury occur.

There have been rare postmarketing reports of fatal and non-fatal hepatic failure in patients taking statins, including fluvastatin. If serious liver injury with clinical symptoms and/or hyperbilirubinemia or jaundice occurs during treatment with LESCOL/LESCOL XL, promptly interrupt therapy. If an alternate etiology is not found do not restart LESCOL/LESCOL XL.

In very rare cases, possibly drug-related hepatitis was observed that resolved upon discontinuation of treatment. Active liver disease or unexplained serum transaminase elevations are contraindications to the use of LESCOL and LESCOL XL [ ]. Caution should be exercised when LESCOL is administered to patients with a history of liver disease or heavy alcohol ingestion [ ]. Such patients should be closely monitored.^1 see Contraindications (4) and Warnings and Precautions (5.2) see Clinical Pharmacology (12.3)

5.3 Endocrine Effects

Increases in HbA1c and fasting serum glucose levels have been reported with HMG-CoA reductase inhibitors, including LESCOL/LESCOL XL.

Statins interfere with cholesterol synthesis and lower circulating cholesterol levels and, as such, might theoretically blunt adrenal or gonadal steroid hormone production.

LESCOL/LESCOL XL exhibited no effect upon non-stimulated cortisol levels and demonstrated no effect upon thyroid metabolism as assessed by measurement of thyroid stimulating hormone (TSH). Small declines in total serum testosterone have been noted in treated groups, but no commensurate elevation in LH occurred, suggesting that the observation was not due to a direct effect upon testosterone production. No effect upon FSH in males was noted. Due to the limited number of premenopausal females studied to date, no conclusions regarding the effect of LESCOL/LESCOL XL upon female sex hormones may be made.

Two clinical studies in patients receiving fluvastatin at doses up to 80 mg daily for periods of 24 to 28 weeks demonstrated no effect of treatment upon the adrenal response to ACTH stimulation. A clinical study evaluated the effect of LESCOL at doses up to 80 mg daily for 28 weeks upon the gonadal response to HCG stimulation. Although the mean total testosterone response was significantly reduced (p<0.05) relative to baseline in the 80 mg group, it was not significant in comparison to the changes noted in groups receiving either 40 mg of LESCOL or placebo.

Patients treated with LESCOL/LESCOL XL who develop clinical evidence of endocrine dysfunction should be evaluated appropriately. Caution should be exercised if a statin or other agent used to lower cholesterol levels is administered to patients receiving other drugs (e.g. ketoconazole, spironolactone, cimetidine) that may decrease the levels of endogenous steroid hormones.

5.4 CNS Toxicity

CNS effects, as evidenced by decreased activity, ataxia, loss of righting reflex, and ptosis were seen in the following animal studies: the 18-month mouse carcinogenicity study at 50 mg/kg/day, the 6-month dog study at 36 mg/kg/day, the 6-month hamster study at 40 mg/kg/day, and in acute, high-dose studies in rats and hamsters (50 mg/kg), rabbits (300 mg/kg) and mice (1500 mg/kg). CNS toxicity in the acute high-dose studies was characterized (in mice) by conspicuous vacuolation in the ventral white columns of the spinal cord at a dose of 5000 mg/kg and (in rats) by edema with separation of myelinated fibers of the ventral spinal tracts and sciatic nerve at a dose of 1500 mg/kg. CNS toxicity, characterized by periaxonal vacuolation, was observed in the medulla of dogs that died after treatment for 5 weeks with 48 mg/kg/day; this finding was not observed in the remaining dogs when the dose level was lowered to 36 mg/kg/day. CNS vascular lesions, characterized by perivascular hemorrhages, edema, and mononuclear cell infiltration of perivascular spaces, have been observed in dogs treated with other members of this drug class. No CNS lesions have been observed after chronic treatment for up to 2 years with fluvastatin in the mouse (at doses up to 350 mg/kg/day), rat (up to 24 mg/kg/day), or dog (up to 16 mg/kg/day).

Prominent bilateral posterior Y suture lines in the ocular lens were seen in dogs after treatment with 1, 8, and 16 mg/kg/day for 2 years.

6 ADVERSE REACTIONS

The following serious adverse reactions are discussed in greater detail in other sections of the label:

- Rhabdomyolysis with myoglobinuria and acute renal failure and myopathy (including myositis) [ ]. see Warnings and Precautions (5.1)
- Liver Enzyme Abnormalities [ ]. see Warnings and Precautions (5.2)

6.1 Clinical Studies Experience in Adult Patients

Because clinical studies on LESCOL/LESCOL XL are conducted in varying study populations and study designs, the frequency of adverse reactions observed in the clinical studies of LESCOL/LESCOL XL cannot be directly compared with that in the clinical studies of other statins and may not reflect the frequency of adverse reactions observed in clinical practice.

In the LESCOL placebo-controlled clinical trials database of 2326 patients treated with LESCOL (age range 18-75 years, 44% women, 94% Caucasians, 4% Blacks, 2% other ethnicities) with a median treatment duration of 24 weeks, 3.4% of patients on LESCOL and 2.3% patients on placebo discontinued due to adverse reactions regardless of causality. The most common adverse reactions that led to treatment discontinuation and occurred at an incidence greater than placebo were: transaminase increased (0.8%), upper abdominal pain (0.3%), dyspepsia (0.3%), fatigue (0.2%) and diarrhea (0.2%).^1

In the LESCOL XL database of controlled clinical trials of 912 patients treated with LESCOL XL (age range 21-87 years, 52% women, 91% Caucasians, 4% Blacks, 5% other ethnicities) with a median treatment duration of 24 weeks, 3.9% of patients on LESCOL XL discontinued due to adverse reactions regardless of causality. The most common adverse reactions that led to treatment discontinuation were abdominal pain (0.7%), diarrhea (0.5%), nausea (0.4%), dyspepsia (0.4%) and chest pain (0.3%).

Clinically relevant adverse experiences occurring in the LESCOL and LESCOL XL controlled studies with a frequency 2%, regardless of causality, included the following: >

Table 1 Clinical adverse events reported in >2% in patients treated with LESCOL/LESCOL XL and at an incidence greater than placebo in placebo-controlled trials regardless of causality (% of patients) Pooled Dosages
 |  | LESCOL N=2326 (%)^1 | Placebo N=960 (%)^1 | LESCOL XL N=912 (%)^2
Musculoskeletal | Myalgia | 5.0 | 4.5 | 3.8
 | Arthritis | 2.1 | 2.0 | 1.3
 | Arthropathy | NA | NA | 3.2
Respiratory | Sinusitis | 2.6 | 1.9 | 3.5
 | Bronchitis | 1.8 | 1.0 | 2.6
Gastrointestinal | Dyspepsia | 7.9 | 3.2 | 3.5
 | Diarrhea | 4.9 | 4.2 | 3.3
 | Abdominal pain | 4.9 | 3.8 | 3.7
 | Nausea | 3.2 | 2.0 | 2.5
 | Flatulence | 2.6 | 2.5 | 1.4
 | Tooth disorder | 2.1 | 1.7 | 1.4
Psychiatric | Insomnia | 2.7 | 1.4 | 0.8
Genitourinary | Urinary tract infection | 1.6 | 1.1 | 2.7
Miscellaneous | Headache | 8.9 | 7.8 | 4.7
 | Influenza-like symptoms | 5.1 | 5.7 | 7.1
 | Accidental Trauma | 5.1 | 4.8 | 4.2
 | Fatigue | 2.7 | 2.3 | 1.6
 | Allergy | 2.3 | 2.2 | 1.0
Controlled trials with LESCOL Capsules (20 and 40 mg daily and 40 mg twice daily) compared to placebo Controlled trials with LESCOL XL 80 mg Tablets as compared to LESCOL Capsules^1
^2

LESCOLIntervention Prevention Study

In the LESCOL Intervention Prevention Study (LIPS), the effect of LESCOL 40 mg, administered twice daily on the risk of recurrent cardiac events was assessed in 1677 patients with CHD who had undergone a percutaneous coronary intervention (PCI) procedure. This was a multicenter, randomized, double-blind, placebo-controlled study, patients were treated with dietary/lifestyle counseling and either LESCOL 40 mg (n=844) or placebo (n=833) given twice daily for a median of 3.9 years [ ]. see Clinical Studies (14.3)

Table 2 Clinical adverse events reported in ≥ 2% in patients treated with LESCOL/LESCOL XL and at an incidence greater than placebo in the LIPS Trial regardless of causality (% of patients)
 |  | LESCOL 40 mg b.i.d. N=822 (%) | Placebo N=818 (%)
Cardiac disorders | Atrial fibrillation | 2.4 | 2.0
Gastrointestinal disorders | Abdominal pain upper | 6.3 | 4.5
 | Constipation | 3.3 | 2.1
 | Dyspepsia | 4.5 | 4.0
 | Gastric disorder | 2.7 | 2.1
 | Nausea | 2.7 | 2.3
General disorders | Fatigue | 4.7 | 3.8
 | Edema peripheral | 4.4 | 2.9
Infections and infestations | Bronchitis | 2.3 | 2.0
 | Nasopharyngitis | 2.8 | 2.1
Musculoskeletal and connective tissue disorders | Arthralgia | 2.1 | 1.8
 | Myalgia | 2.2 | 1.6
 | Pain in extremity | 4.1 | 2.7
Nervous system disorders | Dizziness | 3.9 | 3.5
 | Syncope | 2.4 | 2.2
Respiratory disorders | Dyspnea exertional | 2.8 | 2.4
Vascular disorders | Hypertension | 5.8 | 4.2
 | Intermittent claudication | 2.3 | 2.1

6.2 Clinical Studies Experience in Pediatric Patients

In patients aged <18 years, efficacy and safety have not been studied for treatment periods longer than two years.

In two open-label, uncontrolled studies, 66 boys and 48 girls with heterozygous familial hypercholesterolemia (9-16 years of age, 80% Caucasian, 19% Other [ mixed ethnicity], 1% Asians) were treated with fluvastatin sodium administered as LESCOL capsules 20 mg -40 mg twice daily, or LESCOL XL 80 mg extended-release tablet [ ]. see Clinical Studies (14.2) and Use In Specific Populations (8.4)

6.3 Postmarketing Experience

Because adverse reactions from spontaneous reports are reported voluntarily from a population of uncertain size, it is generally not possible to reliably estimate their frequency or establish a causal relationship to drug exposure. The following effects have been reported with drugs in this class. Not all the effects listed below have necessarily been associated with fluvastatin sodium therapy.

muscle cramps, myalgia, myopathy, rhabdomyolysis, arthralgias, muscle spasms, muscle weakness, myositis. Musculoskeletal:

There have been rare reports of immune-mediated necrotizing myopathy associated with statin use [see ]. Warnings and Precautions (5.1)

dysfunction of certain cranial nerves (including alteration of taste, impairment of extra-ocular movement, facial paresis), tremor, dizziness, vertigo, paresthesia, hypoesthesia, dysesthesia, peripheral neuropathy, peripheral nerve palsy. Neurological:

There have been rare postmarketing reports of cognitive impairment (e.g., memory loss, forgetfulness, amnesia, memory impairment, confusion) associated with statin use. These cognitive issues have been reported for all statins. The reports are generally nonserious, and reversible upon statin discontinuation, with variable times to symptom onset (1 day to years) and symptom resolution (median of 3 weeks).

anxiety, insomnia, depression, psychic disturbances Psychiatric:

An apparent hypersensitivity syndrome has been reported rarely which has included one or more of the following features: anaphylaxis, angioedema, lupus erythematosus-like syndrome, polymyalgia rheumatica, vasculitis, purpura, thrombocytopenia, leukopenia, hemolytic anemia, positive ANA, ESR (erythrocyte sedimentation rate) increase, eosinophilia, arthritis, arthralgia, urticaria, asthenia, photosensitivity reaction, fever, chills, flushing, malaise, dyspnea, toxic epidermal necrolysis, erythema multiforme, including Stevens-Johnson syndrome. Hypersensitivity Reactions:

pancreatitis, hepatitis, including chronic active hepatitis, cholestatic jaundice, fatty change in liver, cirrhosis, fulminant hepatic necrosis, hepatoma, anorexia, vomiting, fatal and non-fatal hepatic failure. Gastrointestinal:

rash, dermatitis, including bullous dermatitis, eczema, alopecia, pruritus, a variety of skin changes (e.g. nodules, discoloration, dryness of skin/mucous membranes, changes to hair/nails). Skin:

gynecomastia, loss of libido, erectile dysfunction. Reproductive:

progression of cataracts (lens opacities), ophthalmoplegia. Eye:

elevated transaminases, alkaline phosphatase, gamma-glutamyl transpeptidase and bilirubin; thyroid function abnormalities. Laboratory abnormalities:

7 DRUG INTERACTIONS

7.1 Cyclosporine

Cyclosporine coadministration increases fluvastatin exposure. Therefore, in patients taking cyclosporine, therapy should be limited to LESCOL 20 mg twice daily [ ]. see Warnings and Precautions (5.1) and Clinical Pharmacology (12.3)

7.2 Fluconazole

Administration of fluvastatin 40 mg single dose to healthy volunteers pre-treated with fluconazole for 4 days results in an increase of fluvastatin exposure. Therefore, in patients taking fluconazole, therapy should be limited to LESCOL 20 mg twice daily [ ]. see Clinical Pharmacology (12.3)

7.3 Gemfibrozil

Due to an increased risk of myopathy/rhabdomyolysis when HMG-CoA reductase inhibitors are coadministered with gemfibrozil, concomitant administration of LESCOL/LESCOL XL with gemfibrozil should be avoided.

7.4 Other Fibrates

Because it is known that the risk of myopathy during treatment with HMG-CoA reductase inhibitors is increased with concurrent administration of other fibrates, LESCOL/LESCOL XL should be administered with caution when used concomitantly with other fibrates [ ]. see Warnings and Precautions (5.1) and Clinical Pharmacology (12.3)

7.5 Niacin

The risk of skeletal muscle effects may be enhanced when LESCOL is used in combination with lipid-modifying doses (≥1 g/day) of niacin; a reduction in LESCOL dosage should be considered in this setting [ ]. see Warnings and Precautions (5.1)

7.6 Glyburide

Concomitant administration of fluvastatin and glyburide increased glyburide exposures. Patients on concomitant therapy of glyburide and fluvastatin should continue to be monitored appropriately [ ]. see Clinical Pharmacology (12.3)

7.7 Phenytoin

Concomitant administration of fluvastatin and phenytoin increased phenytoin exposures. Patients should continue to be monitored appropriately when fluvastatin therapy is initiated or when fluvastatin dose is changed [ ]. see Clinical Pharmacology (12.3)

7.8 Warfarin

Bleeding and/or increased prothrombin times have been reported in patients taking coumarin anticoagulants concomitantly with other HMG-CoA reductase inhibitors. Therefore, patients receiving warfarin-type anticoagulants should have their prothrombin times closely monitored when fluvastatin sodium is initiated or the dosage of fluvastatin sodium is changed.

7.9 Colchicine

Cases of myopathy, including rhabdomyolysis, have been reported with fluvastatin coadministered with colchicine, and caution should be exercised when prescribing fluvastatin with colchicine.

8 USE IN SPECIFIC POPULATIONS

8.1 Pregnancy

Pregnancy Category X

LESCOL/LESCOL XL is contraindicated in women who are or may become pregnant [ ]. see Contraindications (4)

Lipid lowering drugs are contraindicated during pregnancy, because cholesterol and cholesterol derivatives are needed for normal fetal development. Serum cholesterol and triglycerides increase during normal pregnancy. Atherosclerosis is a chronic process, and discontinuation of lipid-lowering drugs during pregnancy should have little impact on long-term outcomes of primary hypercholesterolemia therapy.

There are no adequate and well-controlled studies of use with LESCOL/LESCOL XL during pregnancy. Rare reports of congenital anomalies have been received following intrauterine exposure to other statins. In a review of about 100 prospectively followed pregnancies in women exposed to other statins, the incidences of congenital anomalies, spontaneous abortions, and fetal deaths/stillbirths did not exceed the rate expected in the general population. The number of cases is adequate only to exclude a 3- to 4-fold increase in congenital anomalies over background incidence. In 89% of prospectively followed pregnancies, drug treatment was initiated prior to pregnancy and was discontinued at some point in the first trimester when pregnancy was identified. ^2

Teratology studies with fluvastatin in rats and rabbits showed maternal toxicity at high dose levels, but there was no evidence of embryotoxic or teratogenic potential [ ]. see Non-Clinical Toxicology (13)

LESCOL or LESCOL XL should be administered to women of child-bearing potential only when such patients are highly unlikely to conceive and have been informed of the potential hazards. If a woman becomes pregnant while taking LESCOL or LESCOL XL, the drug should be discontinued and the patient advised again as to the potential hazards to the fetus.

8.3 Nursing Mothers

Based on animal data, fluvastatin is present in breast milk in a 2:1 ratio (milk:plasma). Because of the potential for serious adverse reactions in nursing infants, nursing women should not take LESCOL or LESCOL XL [ ]. see Contraindications (4)

8.4 Pediatric Use

The safety and efficacy of LESCOL and LESCOL XL in children and adolescent patients 9-16 years of age with heterozygous familial hypercholesterolemia have been evaluated in open-label, uncontrolled clinical trials for a duration of two years. The most common adverse events observed were influenza and infections. In these limited uncontrolled studies, there was no detectable effect on growth or sexual maturation in the adolescent boys or on menstrual cycle length in girls [ ]. Adolescent females should be counseled on appropriate contraceptive methods while on LESCOL therapy [ ]. see Clinical Studies (14.2), Adverse Reactions (6.3) and Dosage and Administration (2.2) see Contraindications (4)

8.5 Geriatric Use

Fluvastatin exposures were not significantly different between the nonelderly and elderly populations (age ≥ 65 years) [ ]. Since advanced age (65 years) is a predisposing factor for myopathy, LESCOL/LESCOL XL should be prescribed with caution in the elderly. see Clinical Pharmacology (12.3)>

8.6 Hepatic Impairment

LESCOL and LESCOL XL are contraindicated in patients with active liver disease or unexplained, persistent elevations in serum transaminases [ ]. see Clinical Pharmacology (12.3)

8.7 Renal Impairment

Dose adjustments for mild to moderate renal impairment are not necessary. Fluvastatin has not been studied at doses greater than 40 mg in patients with severe renal impairment; therefore caution should be exercised when treating such patients at higher doses [ ]. see Clinical Pharmacology(12.3)

10 OVERDOSAGE

To date, there has been limited experience with overdosage of fluvastatin. If an overdose occurs, it should be treated symptomatically with laboratory monitoring and supportive measures should be instituted as required. The dialyzability of fluvastatin sodium and of its metabolites in humans is not known at present [ ]. see Warnings and Precautions (5)

In the pediatric population, there have been reports of overdosage with fluvastatin sodium in children including a 2 year-old and the other 3 years of age, either of whom may have possibly ingested fluvastatin sodium. The maximum amount of fluvastatin sodium that could have been ingested was 80 mg (4 x 20 mg capsules). Vomiting was induced by ipecac in both children and no capsules were noted in their emesis. Neither child experienced any adverse symptoms and both recovered from the incident without problems.

In the postmarketing experience there have been reports of accidental ingestion of LESCOL tablets in infants up to 3 years of age. In one case, increased serum CPK values were noted. There have been reports of intentional overdose in adolescents with the development of hepatic enzyme elevations, convulsions and gastroenteritis/vomiting/diarrhea. One case of intentional overdose as suicide attempt in a 15 year-old female reported ingestion of 2,800 mg LESCOL XL with hepatic enzyme elevation.

11 DESCRIPTION

LESCOL is a water-soluble cholesterol lowering agent which acts through the inhibition of 3-hydroxy-3-methylglutaryl-coenzyme A (HMG-CoA) reductase.

Fluvastatin sodium is [ *, *-()]-(±)-7-[3-(4-fluorophenyl)-1-(1-methylethyl)-1 -indol-2-yl]-3,5-dihydroxy-6-heptenoic acid, monosodium salt. The empirical formula of fluvastatin sodium is C H FNO •Na, its molecular weight is 433.46 and its structural formula is: RSEH24254

This molecular entity is the first entirely synthetic HMG-CoA reductase inhibitor, and is in part structurally distinct from the fungal derivatives of this therapeutic class.

Fluvastatin sodium is a white to pale yellow, hygroscopic powder soluble in water, ethanol and methanol. LESCOL is supplied as capsules containing fluvastatin sodium, equivalent to 20 mg or 40 mg of fluvastatin, for oral administration. LESCOL XL is supplied as extended-release tablets containing fluvastatin sodium, equivalent to 80 mg of fluvastatin, for oral administration.

fluvastatin sodium Active Ingredient:

calcium carbonate, gelatin, magnesium stearate, microcrystalline cellulose, pregelatinized starch (corn), red iron oxide, sodium bicarbonate, talc, titanium dioxide, yellow iron oxide, and other ingredients. Inactive Ingredients in capsules:

benzyl alcohol, black iron oxide, butylparaben, carboxymethylcellulose sodium, edetate calcium disodium, methylparaben, propylparaben, silicon dioxide, sodium lauryl sulfate, and sodium propionate. Capsules may also include:

microcrystalline cellulose, hydroxypropyl cellulose, hydroxypropyl methyl cellulose, potassium bicarbonate, povidone, magnesium stearate, yellow iron oxide, titanium dioxide and polyethylene glycol 8000. Inactive Ingredients in extended-release tablets:

12 CLINICAL PHARMACOLOGY

12.1 Mechanism of Action

LESCOL is a competitive inhibitor of HMG-CoA reductase, the rate limiting enzyme that converts 3-hydroxy-3-methylglutaryl-coenzyme A (HMG-CoA) to mevalonate, a precursor of sterols, including cholesterol. The inhibition of cholesterol biosynthesis reduces the cholesterol in hepatic cells, which stimulates the synthesis of LDL receptors and thereby increases the uptake of LDL particles. The end result of these biochemical processes is a reduction of the plasma cholesterol concentration.

12.3 Pharmacokinetics

Absorption:

Following oral administration of the capsule, fluvastatin reaches peak concentrations in less than 1 hour. The absolute bioavailability is 24% (range 9%-50%) after administration of a 10 mg dose.

At steady state, administration of fluvastatin with the evening meal results in a 50% decrease in C , an 11% decrease in AUC, and a more than two-fold increase in t as compared to administration 4 hours after the evening meal. No significant differences in the lipid-lowering effects were observed between the two administrations. After single or multiple doses above 20 mg, fluvastatin exhibits saturable first-pass metabolism resulting in more than dose proportional plasma fluvastatin concentrations.maxmax

Fluvastatin administered as LESCOL XL 80 mg tablets reaches peak concentration in approximately 3 hours under fasting conditions, after a low-fat meal, or 2.5 hours after a low-fat meal. The mean relative bioavailability of the XL tablet is approximately 29% (range: 9%-66%) compared to that of the LESCOL immediate-release capsule administered under fasting conditions. Administration of a high-fat meal delayed the absorption (T : 6h) and increased the bioavailability of the XL tablet by approximately 50%. However, the maximum concentration of LESCOL XL seen after a high-fat meal is less than the peak concentration following a single dose or twice daily dose of the 40 mg LESCOL capsule.max

Distribution:

Fluvastatin is 98% bound to plasma proteins. The mean volume of distribution (VD) is estimated at 0.35 L/kg. At therapeutic concentrations, the protein binding of fluvastatin is not affected by warfarin, salicylic acid and glyburide.ss

Metabolism:

Fluvastatin is metabolized in the liver, primarily via hydroxylation of the indole ring at the 5- and 6-positions. N-dealkylation and beta-oxidation of the side-chain also occurs. The hydroxy metabolites have some pharmacologic activity, but do not circulate in the blood. Fluvastatin has two enantiomers. Both enantiomers of fluvastatin are metabolized in a similar manner.

In vitro data indicate that fluvastatin metabolism involves multiple Cytochrome P450 (CYP) isozymes. CYP2C9 isoenzyme is primarily involved in the metabolism of fluvastatin (approximately 75%), while CYP2C8 and CYP3A4 isoenzymes are involved to a much less extent, i.e. approximately 5% and approximately 20%, respectively.

Excretion:

Following oral administration, fluvastatin is primarily (about 90%) excreted in the feces as metabolites, with less than 2% present as unchanged drug. Approximately 5% of a radiolabeled oral dose were recovered in urine. The elimination half-life (t) of fluvastatin is approximately 3 hours. 1/2

Specific Populations

Renal Impairment:

In patients with moderate to severe renal impairment (CL 10-40 mL/min), AUC and C increased approximately 1.2-fold after administration of a single dose of 40 mg fluvastatin compared to healthy volunteers. In patients with end-stage renal disease on hemodialysis, the AUC increased by approximately 1.5-fold. LESCOL XL was not evaluated in patients with renal impairment. However, systemic exposures after administration of LESCOL XL are lower than after the 40 mg immediate release capsule.Crmax

Hepatic Impairment:

In patients with hepatic impairment due to liver cirrhosis, fluvastatin AUC and C increased approximately 2.5- fold compared to healthy subjects after administration of a single 40 mg dose. The enantiomer ratios of the two isomers of fluvastatin in hepatic impairment patients were comparable to those observed in healthy subjects.max

Geriatric:

Plasma levels of fluvastatin are not significantly different in patients age > 65 years compared to patients age 21 to 49 years.

Gender:

In a study evaluating the effect of age and gender on fluvastatin pharmacokinetics, there were no significant differences in fluvastatin exposures between males and females, except between younger females and younger males (both ages 21-49 years), where there was an approximate 30% increase in AUC in females. Adjusting for body weight decreases the magnitude of the differences seen. For LESCOL XL, the AUC increases 67% and 77% for women compared to men under fasted and high- fat meal fed conditions, respectively.

Pediatric:

Pharmacokinetic data in the pediatric population are not available.

Drug-Drug Interactions:

Data from drug-drug interactions studies involving coadministration of gemfibrozil, niacin, itraconazole, erythromycin, tolbutamide or clopidogrel indicate that the PK disposition of fluvastatin is not significantly altered when fluvastatin is coadministered with any of these drugs.

The below listed drug interaction information is derived from studies using LESCOL. Similar studies have not been conducted using the LESCOL XL tablet.

Table 3 Effect of Co-administered Drugs on Fluvastatin Systemic Exposure
Co-administered drug and dosing regimen | Fluvastatin
 | Dose (mg)* | Change in AUC** | Change in Cmax**
Cyclosporine – stable dose (b.i.d.)† | 20 mg QD for 14 weeks | ↑ 90% | ↑ 30%
Fluconazole 400 mg QD day 1, 200 mg b.i.d. day 2- 4† | 40 mg QD | ↑ 84% | ↑ 44%
Cholestyramine 8 g QD | 20 mg QD administered 4 hrs after a meal plus cholestyramine | ↓ 51% | ↓ 83%
Rifampicin 600 mg QD for 6 days | 20 mg QD | ↓ 53% | ↓ 42%
Cimetidine 400 mg b.i.d. for 5 days, QD on Day 6 | 20 mg QD | ↑ 30% | ↑ 40%
Ranitidine 150 mg b.i.d. for 5 days, QD on Day 6 | 20 mg QD | ↑ 10% | ↑ 50%
Omeprazole 40 mg QD for 6 days | 20 mg QD | ↑ 20% | ↑ 37%
Phenytoin 300 mg QD | 40 mg b.i.d. for 5 days | ↑ 40 % | ↑ 27%
Propranolol 40 mg b.i.d. for 3.5 days | 40 mg QD | ↓ 5% | No change
Digoxin 0.1 – 0.5 mg QD for 3 weeks | 40 mg QD | No change | ↑ 11%
Diclofenac 25 mg QD | 40 mg QD for 8 days | ↑50 % | ↑ 80%
Glyburide 5 – 20 mg QD for 22 days | 40 mg b.i.d. for 14 days | ↑ 51% | ↑ 44%
Warfarin 30 mg QD | 40 mg QD for 8 days | ↑ 30% | ↑ 67%
Clopidogrel 300 mg loading dose on day 10, 75 mg QD on days 11-19 | 80 mg XL QD for 19 days | ↓ 2% | ↑ 27%

*Single dose unless otherwise noted

**Mean ratio (with/without coadministered drug and no change = 1-fold) or % change (with/without coadministered drug and no change = 0%); symbols of ↑ and ↓ indicate the exposure increase and decrease, respectively.

† Considered clinically significant [see Dosage and Administration (2) and Drug Interactions (7)]

Data from drug-drug interaction studies involving fluvastatin and coadministration of either gemfibrozil, tolbutamide or losartan indicate that the PK disposition of either gemfibrozil, tolbutamide or losartan is not significantly altered when coadministered with fluvastatin.

Table 4 Effect of Fluvastatin Co-Administration on Systemic Exposure of Other Drugs
Fluvastatin dosage regimen | Co-administered drug
 | Name and Dose (mg)* | Change in AUC** | Change in Cmax**
40 mg QD for 5 days | Phenytoin 300 mg QD† | ↑ 20% | ↑ 5%
40 mg b.i.d. for 21 days | Glyburide 5 – 20 mg QD for 22 days † | ↑ 70% | ↑ 50%
40 mg QD for 8 days | Diclofenac 25 mg QD | ↑ 25% | ↑ 60%
40 mg QD for 8 days | Warfarin 30 mg QD | S-warfarin: ↑ 7% | ↑ 10%
 |  | R-warfarin: no change | ↑ 6%

*Single dose unless otherwise noted

**Mean ratio (with/without coadministered drug and no change = 1-fold) or % change (with/without coadministered drug and no change = 0%); symbols of ↑ and ↓ indicate the exposure increase and decrease, respectively.

† Considered clinically significant [ ] see Dosage and Administration (2) and Drug Interactions (7)

13 NONCLINICAL TOXICOLOGY

13.1 Carcinogenesis, Mutagenesis, Impairment of Fertility

A 2-year study was performed in rats at dose levels of 6, 9, and 18-24 (escalated after 1 year) mg/kg/day. These treatment levels represented plasma drug levels of approximately 9, 13, and 26-35 times the mean human plasma drug concentration after a 40 mg oral dose. A low incidence of forestomach squamous papillomas and 1 carcinoma of the forestomach at the 24 mg/kg/day dose level was considered to reflect the prolonged hyperplasia induced by direct contact exposure to fluvastatin sodium rather than to a systemic effect of the drug. In addition, an increased incidence of thyroid follicular cell adenomas and carcinomas was recorded for males treated with 18-24 mg/kg/day. The increased incidence of thyroid follicular cell neoplasm in male rats with fluvastatin sodium appears to be consistent with findings from other HMG-CoA reductase inhibitors. In contrast to other HMG-CoA reductase inhibitors, no hepatic adenomas or carcinomas were observed.

The carcinogenicity study conducted in mice at dose levels of 0.3, 15 and 30 mg/kg/day revealed, as in rats, a statistically significant increase in forestomach squamous cell papillomas in males and females at 30 mg/kg/day and in females at 15 mg/kg/day. These treatment levels represented plasma drug levels of approximately 0.05, 2, and 7 times the mean human plasma drug concentration after a 40 mg oral dose.

No evidence of mutagenicity was observed in vitro, with or without rat-liver metabolic activation, in the following studies: microbial mutagen tests using mutant strains of or ; malignant transformation assay in BALB/3T3 cells; unscheduled DNA synthesis in rat primary hepatocytes; chromosomal aberrations in V79 Chinese Hamster cells; HGPRT V79 Chinese Hamster cells. In addition, there was no evidence of mutagenicity in vivo in either a rat or mouse micronucleus test. Salmonellatyphimurium Escherichia coli

In a study in rats at dose levels for females of 0.6, 2 and 6 mg/kg/day and at dose levels for males of 2, 10 and 20 mg/kg/day, fluvastatin sodium had no adverse effects on the fertility or reproductive performance.

Seminal vesicles and testes were small in hamsters treated for 3 months at 20 mg/kg/day (approximately three times the 40 mg human daily dose based on surface area, mg/m). There was tubular degeneration and aspermatogenesis in testes as well as vesiculitis of seminal vesicles. Vesiculitis of seminal vesicles and edema of the testes were also seen in rats treated for 2 years at 18 mg/kg/day (approximately 4 times the human C achieved with a 40 mg daily dose).^2max

Fluvastatin sodium produced delays in skeletal development in rats at doses of 12 mg/kg/day and in rabbits at doses of 10 mg/kg/day. Malaligned thoracic vertebrae were seen in rats at 36 mg/kg, a dose that produced maternal toxicity. These doses resulted in 2 times (rat at 12 mg/kg) or 5 times (rabbit at 10 mg/kg) the 40 mg human exposure based on mg/m surface area. A study in which female rats were dosed during the third trimester at 12 and 24 mg/kg/day resulted in maternal mortality at or near term and postpartum. In addition, fetal and neonatal lethality were apparent. No effects on the dam or fetus occurred at 2 mg/kg/day. A second study at levels of 2, 6, 12 and 24 mg/kg/day confirmed the findings in the first study with neonatal mortality beginning at 6 mg/kg. A modified Segment III study was performed at dose levels of 12 or 24 mg/kg/day with or without the presence of concurrent supplementation with mevalonic acid, a product of HMG-CoA reductase which is essential for cholesterol biosynthesis. The concurrent administration of mevalonic acid completely prevented the maternal and neonatal mortality but did not prevent low body weights in pups at 24 mg/kg on days 0 and 7 postpartum. ^2

14 CLINICAL STUDIES

14.1 Hypercholesterolemia (Heterozygous Familial and Nonfamilial) and Mixed Dyslipidemia

In 12 placebo-controlled studies in patients with primary hypercholesterolemia and mixed dyslipidemia, LESCOL was administered to 1621 patients in daily dose regimens of 20 mg, 40 mg, and 80 mg (40 mg twice daily) for at least 6 weeks duration (Table 5). After 24 weeks of treatment, treatment with LESCOL resulted in significantly reduced plasma LDL-C, TC, TG, and Apo B compared to placebo and was associated with variable increases in HDL-C across the dose range.

LESCOL XL has been studied in five controlled studies of patients with primary hypercholesterolemia and mixed dyslipidemia. LESCOL XL was administered to over 900 patients in trials from 4 to 26 weeks in duration. In the three largest of these studies, LESCOL XL given as a single daily dose of 80 mg significantly reduced Total-C, LDL-C, TG and Apo B and resulted in increases in HDL-C (Table 5).

In patients with primary mixed dyslipidemia as defined by baseline plasma TG levels ≥200 mg/dL and <400 mg/dL, treatment with LESCOL/LESCOL XL produced significant decreases in Total-C, LDL-C, TG and Apo B and variable increases in HDL-C (Table 5).

Table 5 Median Percent Change in Lipid Parameters from Baseline to Week 24 Endpoint All Placebo-Controlled Studies (LESCOL) and Active Controlled Trials (LESCOL XL)
 | Total Chol |  | TG |  | LDL |  | Apo B |  | HDL
Dose | N | % ∆ | N | % ∆ | N | % ∆ | N | % ∆ | N | % ∆
All Patients
LESCOL 20 mg^1 | 747 | -17 | 747 | -12 | 747 | -22 | 114 | -19 | 747 | +3
LESCOL 40 mg^1 | 748 | -19 | 748 | -14 | 748 | -25 | 125 | -18 | 748 | +4
LESCOL 40 mg twice daily^1 | 257 | -27 | 257 | -18 | 257 | -36 | 232 | -28 | 257 | +6
LESCOL XL 80 mg^2 | 750 | -25 | 750 | -19 | 748 | -35 | 745 | -27 | 750 | +7
Baseline TG ≥200 mg/dL
LESCOL 20 mg^1 | 148 | -16 | 148 | -17 | 148 | -22 | 23 | -19 | 148 | +6
LESCOL 40 mg^1 | 179 | -18 | 179 | -20 | 179 | -24 | 47 | -18 | 179 | +7
LESCOL 40 mg twice daily^1 | 76 | -27 | 76 | -23 | 76 | -35 | 69 | -28 | 76 | +9
LESCOL XL 80 mg^2 | 239 | -25 | 239 | -25 | 237 | -33 | 235 | -27 | 239 | +11

^1Data for LESCOL from 12 placebo-controlled trials

^2Data for LESCOL XL 80 mg tablet from three 24- week controlled trials

14.2 Heterozygous Familial Hypercholesterolemia in Pediatric Patients

LESCOL was studied in two open-label, uncontrolled, dose-titration studies. The first study enrolled 29 pre-pubertal boys, 9-12 years of age, who had an LDL-C level >90th percentile for age and one parent with primary hypercholesterolemia and either a family history of premature ischemic heart disease or tendon xanthomas. The mean baseline LDL-C was 226 mg/dL (range: 137-354 mg/dL). All patients were started on LESCOL capsules 20 mg daily with dose adjustments every 6 weeks to 40 mg daily then 80 mg daily (40 mg b.i.d.) to achieve an LDL-C goal between 96.7 – 123.7 mg/dL. Endpoint analyses were performed at Year 2. LESCOL decreased plasma levels of Total-C and LDL-C by 21% and 27%, respectively. The mean achieved LDL-C was 161 mg/dL (range: 74-336 mg/dL).

The second study enrolled 85 male and female patients, 10 to 16 years of age, who had an LDL-C >190 mg/dL or LDL-C >160 mg/dL and one or more risk factors for coronary heart disease, or LDL-C >160 mg/dL and a proven LDL-receptor defect. The mean baseline LDL-C was 225 mg/dL (range: 148-343 mg/dL). All patients were started on LESCOL capsules 20 mg daily with dose adjustments every 6 weeks to 40 mg daily then 80 mg daily (LESCOL 80 mg XL tablet) to achieve an LDL-C goal of <130 mg/dL. Endpoint analyses were performed at Week 114. LESCOL decreased plasma levels of Total-C and LDL-C by 22% and 28%, respectively. The mean achieved LDL-C was 159 mg/dL (range: 90-295 mg/dL).

The majority of patients in both studies (83% in the first study and 89% in the second study) were titrated to the maximum daily dose of 80 mg. At study endpoint, 26% to 30% of patients in both studies achieved a targeted LDL-C goal of <130 mg/dL. The long-term efficacy of LESCOL or LESCOL XL therapy in childhood to reduce morbidity and mortality in adulthood has not been established.

14.3 Secondary Prevention of Cardiovascular Disease

In the LESCOL Intervention Prevention Study (LIPS), the effect of LESCOL 40 mg administered twice daily on the risk of recurrent cardiac events (time to first occurrence of cardiac death, nonfatal myocardial infarction, or revascularization) was assessed in 1677 patients with CHD who had undergone a percutaneous coronary intervention (PCI) procedure (mean time from PCI to randomization=3 days). In this multicenter, randomized, double-blind, placebo-controlled study, patients were treated with dietary/lifestyle counseling and either LESCOL 40 mg (n=844) or placebo (n=833) given twice daily for a median of 3.9 years. The study population was 84% male, 98% Caucasian, with 37% >65 years of age. Mean baseline lipid concentrations were: total cholesterol 201 mg/dL, LDL-C 132 mg/dL, triglycerides 70 mg/dL and HDL-C 39 mg/dL.

LESCOL significantly reduced the risk of recurrent cardiac events (Figure 1) by 22% (p=0.013, 181 patients in the LESCOL group vs. 222 patients in the placebo group). Revascularization procedures comprised the majority of the initial recurrent cardiac events (143 revascularization procedures in the LESCOL group and 171 in the placebo group). Consistent trends in risk reduction were observed in patients >65 years of age.

Figure 1 Primary Endpoint – Recurrent Cardiac Events (Cardiac Death, Nonfatal MI or Revascularization Procedure) (ITT Population)

Outcome data for the LESCOL Intervention Prevention Study are shown in Figure 2. After exclusion of revascularization procedures (CABG and repeat PCI) occurring within the first 6 months of the initial procedure involving the originally instrumental site, treatment with LESCOL was associated with a 32% (p=0.002) reduction in risk of late revascularization procedures (CABG or PCI occurring at the original site >6 months after the initial procedure, or at another site).

Figure 2 LESCOL® Intervention Prevention Study - Primary and Secondary Endpoints

In the Lipoprotein and Coronary Atherosclerosis Study (LCAS), the effect of LESCOL therapy on coronary atherosclerosis was assessed by quantitative coronary angiography (QCA) in patients with CAD and mild to moderate hypercholesterolemia (baseline LDL-C range 115-190 mg/dL). In this randomized double-blind, placebo- controlled trial, 429 patients were treated with conventional measures (Step 1 AHA Diet) and either LESCOL 40 mg/day or placebo. In order to provide treatment to patients receiving placebo with LDL-C levels ≥160 mg/dL at baseline, adjunctive therapy with cholestyramine was added after Week 12 to all patients in the study with baseline LDL-C values of ≥160 mg/dL which were present in 25% of the study population. Quantitative coronary angiograms were evaluated at baseline and 2.5 years in 340 (79%) angiographic evaluable patients.

Compared to placebo, LESCOL significantly slowed the progression of coronary atherosclerosis as measured by within-patient per-lesion change in minimum lumen diameter (MLD), the primary endpoint (Figure 3 below), percent diameter stenosis (Figure 4), and the formation of new lesions (13% of all fluvastatin patients versus 22% of all placebo patients). A significant difference in favor of LESCOL was found between all fluvastatin and all placebo patients in the distribution among the three categories of definite progression, definite regression, and mixed or no change. Beneficial angiographic results (change in MLD) were independent of patients’ gender and consistent across a range of baseline LDL-C levels.

Figure 3 Change in Minimum Lumen Diameter (mm)
Figure 4 Change in % Diameter Stenosis

15 REFERENCES

1. National Cholesterol Education Program (NCEP): Highlights of the Report of the Expert Panel on Blood Cholesterol Levels in Children and Adolescents. . 89(3):495-501.1992. Pediatrics

2. Manson, J.M., Freyssinges, C., Ducrocq, M.B., Stephenson, W.P., Postmarketing Surveillance of Lovastatin and Simvastatin Exposure During Pregnancy, 10(6): 439-446, 1996. Reproductive Toxicology,

16 HOW SUPPLIED/STORAGE AND HANDLING

NDC:68151-4471-1 in a PACKAGE of 1 TABLET, EXTENDED RELEASES

17 PATIENT COUNSELING INFORMATION

Information for Patients

Patients taking LESCOL/LESCOL XL should be advised that high cholesterol is a chronic condition and they should adhere to their medication along with their National Cholesterol Education Program (NCEP)-recommended diet, a regular exercise program, and periodic testing of a fasting lipid panel to determine goal attainment.

Patients should be advised about substances they should not take concomitantly with LESCOL/LESCOL XL [see Warnings and Precautions (5.1)]. Patients should also be advised to inform other healthcare professionals prescribing a new medication thatthey are taking LESCOL/LESCOLXL.

17.1 Muscle Pain

Patients starting therapy with LESCOL/LESCOL XL should be advised of the risk of myopathy and told to report promptly any unexplained muscle pain, tenderness or weakness, particularly if accompanied by malaise or fever or if these muscle signs or symptoms persist after discontinuing LESCOL/LESCOL XL.

17.2 Liver Enzymes

It is recommended that liver enzyme tests be performed before the initiation of LESCOL/LESCOL XL and if signs or symptoms of liver injury occur. All patients treated with LESCOL/LESCOL XL should be advised to report promptly any symptoms that may indicate liver injury, including fatigue, anorexia, right upper abdominal discomfort, dark urine or jaundice.

17.3 Pregnancy

Women of childbearing age should be advised to use an effective method of birth control to prevent pregnancy while using LESCOL/LESCOL XL. Discuss future pregnancy plans with your patients, and discuss when to stop taking LESCOL/LESCOL XL if they are trying to conceive. Patients should be advised that if they become pregnant they should stop taking LESCOL/LESCOL XL and call their healthcare professional.

17.4 Breastfeeding

Women who are breastfeeding should not use LESCOL/LESCOL XL. Patients who have a lipid disorder and are breastfeeding should be advised to discuss the options with their healthcare professional.

T2012-204 October 2012

FDA-Approved Patient Labeling

LESCOL (fluvastatin sodium) Capsules®

20 mg, 40 mg

LESCOL XL (fluvastatin sodium) Extended-Release Tablets®

80 mg

Rx Only

You must read and follow all instructions before using LESCOL or LESCOL XL.

Read the Patient Information every time you or a family member gets LESCOL or LESCOL XL. There may be new information. This Patient Information does not take the place of talking with your doctor about your medical condition or treatment. If you have any questions about LESCOL or LESCOL XL, ask your doctor or pharmacist.

What are LESCOL and LESCOL XL?

LESCOL and LESCOL XL are prescription medicines called "statins" that lower cholesterol in your blood. They lower the "bad" cholesterol and triglycerides in your blood. They can raise your "good" cholesterol as well.

LESCOL and LESCOL XL are for people whose cholesterol does not come down enough with exercise and a low-fat diet alone.

LESCOL and LESCOL XL may be used in patients with heart disease (coronary artery disease) to:

- lower the chances of heart problems which would require procedures to help restore blood flow to the heart.
- slow the buildup of too much cholesterol in the arteries of the heart.

Treatment with LESCOL or LESCOL XL has not been shown to prevent heart attacks or stroke.

LESCOL and LESCOL XL have the same active ingredient, fluvastatin. However, LESCOL is a capsule that is taken one or two times a day and LESCOL XL is an extended-release tablet that is only taken one time a day.

Who should not take LESCOL or LESCOL XL?

Do not take LESCOL or LESCOL XL if you:

- are pregnant or think you may be pregnant, or are planning to become pregnant. LESCOL and LESCOL XL may harm your unborn baby. If you get pregnant, stop taking LESCOL or LESCOL XL and call your doctor right away.
- are breast-feeding. LESCOL and LESCOL XL can pass into your breast milk and may harm your baby
- have liver problems
- are allergic to LESCOL or LESCOL XL or any of its ingredients. The active ingredient in LESCOL and LESCOL XL is fluvastatin. See the end of this leaflet for a complete list of ingredients in LESCOL and LESCOL XL.

LESCOL and LESCOL XL have not been studied in children under 9 years of age.

Before taking LESCOL or LESCOL XL, tell your doctor if you:

- have muscle aches or weakness
- drink more than 2 glasses of alcohol daily
- have diabetes
- have a thyroid problem
- have kidney problems

Some medicines should not be taken with LESCOL or LESCOL XL. Tell your doctor about all the medicines you take, including prescription and non-prescription medicines, vitamins and herbal supplements. LESCOL and LESCOL XL and certain other medicines can interact causing serious side effects. Especially tell your doctor if you take medicines for:

- your immune system
- cholesterol
- infections
- heart failure
- seizures
- diabetes
- heartburn or stomach ulcers

Know all the medicines you take. Keep a list of all the medicines you take with you to show your doctor and pharmacist.

How should I take LESCOL or LESCOL XL?

- Your doctor will prescribe the medicine that is right for you. Take LESCOL or LESCOL XL exactly as prescribed. Do not change your dose or stop LESCOL or LESCOL XL without talking to your doctor. Your doctor may do blood tests to check your cholesterol levels during treatment with LESCOL and LESCOL XL. Your dose of LESCOL or LESCOL XL may be changed based on these blood test results.
- LESCOL XL tablets may be taken at any time of the day. Take LESCOL capsules at the same time every evening. When LESCOL capsules are taken twice daily, the capsules may be taken once in the morning and once in the evening. LESCOL and LESCOL XL can be taken with or without food.
- LESCOL XL tablets must be swallowed whole with a liquid. Do not break, crush or chew LESCOL XL tablets or open LESCOL capsules. Tell your doctor if you cannot swallow tablets whole. You may need LESCOL capsules or a different medicine instead of LESCOL XL tablets.
- Your doctor should start you on a low-fat and low-cholesterol diet before giving you LESCOL or LESCOL XL. Stay on this low-fat and low-cholesterol diet while taking LESCOL or LESCOL XL.
- If you miss a dose of LESCOL or LESCOL XL take it as soon as you remember. Do not take LESCOL or LESCOL XL if it has been more than 12 hours since your last dose. Wait and take the next dose at your regular time. Do not take 2 doses of LESCOL or LESCOL XL at the same time. ,
- If you take too much LESCOL or LESCOL XL or overdose, call your doctor or Poison Control Center right away. Or, go to the nearest emergency room.

What should I avoid while taking LESCOL or LESCOL XL?

- Talk to your doctor before you start any new medicines. This includes prescription and nonprescription medicines, vitamins and herbal supplements. LESCOL and LESCOL XL and certain other medicines can interact causing serious side effects.
- Do not get pregnant. If you get pregnant, stop taking LESCOL or LESCOL XL right away and call your doctor.

What are the possible side effects of LESCOL and LESCOL XL?

When taking LESCOL and LESCOL XL, some patients may develop serious side effects, including:

Call your health care professional right away if you experience unexplained muscle pain, tenderness, or weakness especially with fever. This may be an early sign of a rare muscle problem that could lead to serious kidney problems. muscle problems.

The risk of muscle problems is greater in people who are 65 years of age or older, or who already have thyroid or kidney problems. The chance of muscle problems may be increased if you are taking certain other medicines with LESCOL or LESCOL XL.

If you have muscle problems that do not go away even after your health care professional has advised you to stop taking LESCOL or LESCOL XL, notify your health care professional. Your health care professional may do further tests to diagnose the cause of your muscle problems.

Your doctor should do blood tests to check your liver before you start taking LESCOL or LESCOL XL, and if you have symptoms of liver problems while you take LESCOL or LESCOL XL. Call your doctor right away if you have the following symptoms of liver problems: liver problems.

- feel tired or weak
- loss of appetite
- upper belly pain
- dark amber colored urine
- yellowing of your skin or the whites of your eyes

The most common side effects of LESCOL or LESCOL XL are headache, upset stomach and stomach pain, diarrhea, flu-like symptoms, muscle pain, sinus infection, tiredness, or trouble sleeping. These side effects are usually mild and may go away. The following additional side effects have been reported with LESCOL/LESCOL XL: memory loss, and confusion.

Talk to your doctor or pharmacist if you have side effects that bother you or that will not go away.

These are not all the side effects of LESCOL and LESCOL XL. Ask your doctor or pharmacist for a complete list.

How should I store LESCOL and LESCOL XL?

- Store LESCOL and LESCOL XL at room temperature, 59° to 86° F (15° to 30° C). Protect from light.
- Do not keep medicine that is out of date or that you no longer need.
- Keep LESCOL and LESCOL XL out of the reach of children. Be sure that if you throw medicines away, it is out of the reach of children.

General information about LESCOL and LESCOL XL

Medicines are sometimes prescribed for conditions that are not mentioned in patient information leaflets. Do not use LESCOL or LESCOL XL for a condition for which it was not prescribed. Do not give LESCOL or LESCOL XL to other people, even if they have the same problem you have; it may harm them.

For more information, you can also visit the Novartis Internet site at or call the Novartis help line at 1-888-669-6682. www.LESCOLXL.com

What are the ingredients in LESCOL and LESCOL XL?

fluvastatin sodium Active Ingredient:

Inactive Ingredients:

calcium carbonate, gelatin, magnesium stearate, microcrystalline cellulose, pregelatinized starch (corn), red iron oxide, sodium bicarbonate, talc, titanium dioxide, yellow iron oxide, and other ingredients. The capsules may also contain benzyl alcohol, black iron oxide, butylparaben, carboxymethylcellulose sodium, edetate calcium disodium, methylparaben, propylparaben, silicon dioxide, sodium lauryl sulfate, and sodium propionate. LESCOL Capsules:

microcrystalline cellulose, hydroxypropyl cellulose, hydroxypropyl methylcellulose, potassium bicarbonate, povidone, magnesium stearate, yellow iron oxide, titanium dioxide and polyethylene glycol 8000. LESCOL XL Tablets:

Distributed by:

Novartis Pharmaceuticals Corporation

East Hanover, New Jersey 07936

© Novartis

T2012-205 October 2012